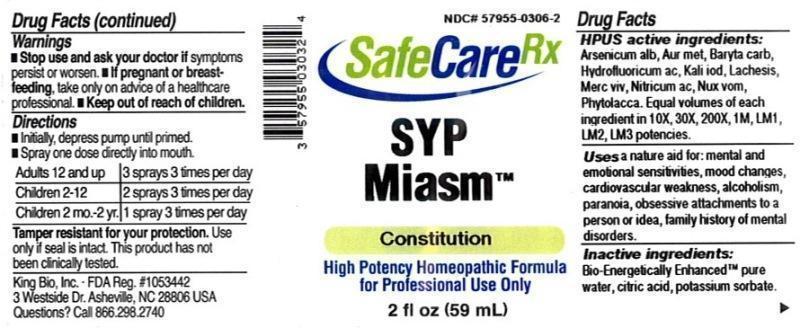 DRUG LABEL: SYP Miasm
NDC: 57955-0306 | Form: LIQUID
Manufacturer: King Bio Inc.
Category: homeopathic | Type: HUMAN OTC DRUG LABEL
Date: 20150728

ACTIVE INGREDIENTS: ARSENIC TRIOXIDE 10 [hp_X]/59 mL; GOLD 10 [hp_X]/59 mL; BARIUM CARBONATE 10 [hp_X]/59 mL; HYDROFLUORIC ACID 10 [hp_X]/59 mL; POTASSIUM IODIDE 10 [hp_X]/59 mL; LACHESIS MUTA VENOM 10 [hp_X]/59 mL; MERCURY 10 [hp_X]/59 mL; NITRIC ACID 10 [hp_X]/59 mL; STRYCHNOS NUX-VOMICA SEED 10 [hp_X]/59 mL; PHYTOLACCA AMERICANA ROOT 10 [hp_X]/59 mL
INACTIVE INGREDIENTS: WATER; ANHYDROUS CITRIC ACID; POTASSIUM SORBATE

SYP Miasm™

ACTIVE INGREDIENT

Drug Facts__________________________________________________________________________________________________________

HPUS active ingredients: Arsenicum album, Aurum metallicum, Baryta carbonica, Hydrofluoricum acidum, Kali iodatum, Lachesis mutus, Mercurius vivus, Nitricum acidum, Nux vomica, Phytolacca decandra. Equal volumes of each ingredient in 10X, 30X, 200X, 1M, LM1, LM2, LM3 potencies.

INDICATIONS AND USAGE

Uses a natural aid for: mental and emotional sensitivities, mood changes, cardiovascular weakness, alcoholism, paranoia, obsessive attachments to person or idea, family history of mental disorders.

Inactive Ingredients:

Bio-Energetically Enhanced™ pure water, citric acid and potassium sorbate.

Warnings

- Stop use and ask your doctor if symptoms persist or worsen.
- If pregnant or breast-feeding, take only on advice of a healthcare professional.

- Keep out of reach of children.

Directions

- Initially, depress pump until primed.
- Spray one dose directly into mouth.
- Adults 12 and up: 3 sprays 3 times per day.
- Children 2-12: 2 sprays 3 times per day.
- Children 2mo.-2 yr: 1 spray 3 times per day.

OTHER SAFETY INFORMATION

Tamper resistant for your protection. Use only if safety seal is intact. This product has not been clinically tested.

PURPOSE

Uses a natural aid for relief of:

- mental and emotional sensitivities
- mood changes
- cardiovascular weakness
- alcoholism
- paranoia
- obsessive attachments to person or idea
- family history of mental disorders